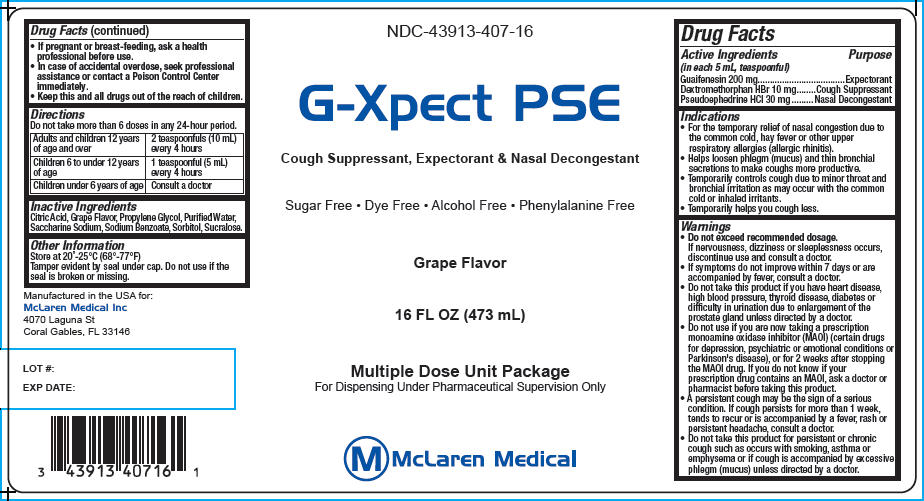 DRUG LABEL: G-Xpect PSE
NDC: 43913-407 | Form: LIQUID
Manufacturer: McLaren Medical
Category: otc | Type: HUMAN OTC DRUG LABEL
Date: 20140423

ACTIVE INGREDIENTS: Dextromethorphan Hydrobromide 10 mg/5 mL; Guaifenesin 200 mg/5 mL; Pseudoephedrine Hydrochloride 30 mg/5 mL
INACTIVE INGREDIENTS: Sodium Benzoate; Citric Acid Monohydrate; Sorbitol; Saccharin Sodium; Sucralose; Propylene Glycol; Water

G-Xpect PSE

Drug Facts

ACTIVE INGREDIENT

Active Ingredients (in each 5 mL, teaspoonful) | Purpose
Guaifenesin 200 mg | Expectorant
Dextromethorphan HBr 10 mg | Cough Suppressant
Pseudoephedrine HCI 30 mg | Nasal Decongestant

Indications

- For the temporary relief of nasal congestion due to the common cold, hay fever or other upper respiratory allergies (allergic rhinitis).
- Helps loosen phlegm (mucus) and thin bronchial secretions to make coughs more productive.
- Temporarily controls cough due to minor throat and bronchial irritation as may occur with the common cold or inhaled irritants.
- Temporarily helps you cough less.

Warnings

STOP USE

- Do not exceed recommended dosage.
  If nervousness, dizziness or sleeplessness occurs, discontinue use and consult a doctor.
- If symptoms do not improve within 7 days or are accompanied by fever, consult a doctor.

DO NOT USE

- Do not take this product if you have heart disease, high blood pressure, thyroid disease, diabetes or difficulty in urination due to enlargement of the prostate gland unless directed by a doctor.
- Do not use if you are now taking a prescription monoamine oxidase inhibitor (MAOI) (certain drugs for depression, psychiatric or emotional conditions or Parkinson's disease), or for 2 weeks after stopping the MAOI drug. If you do not know if your prescription drug contains an MAOI, ask a doctor or pharmacist before taking this product.

ASK DOCTOR

- A persistent cough may be the sign of a serious condition. If cough persists for more than 1 week, tends to recur or is accompanied by a fever, rash or persistent headache, consult a doctor.

DO NOT USE

- Do not take this product for persistent or chronic cough such as occurs with smoking, asthma or emphysema or if cough is accompanied by excessive phlegm (mucus) unless directed by a doctor.

PREGNANCY OR BREAST FEEDING

- If pregnant or breast-feeding, ask a health professional before use.

ASK DOCTOR/PHARMACIST

- In case of accidental overdose, seek professional assistance or contact a Poison Control Center immediately.

KEEP OUT OF REACH OF CHILDREN

- Keep this and all drugs out of the reach of children.

Directions

Do not take more than 6 doses in any 24-hour period.

Adults and children 12 years of age and over | 2 teaspoonfuls (10 mL) every 4 hours
Children 6 to under 12 years of age | 1 teaspoonful (5 mL) every 4 hours
Children under 6 years of age | Consult a doctor

Inactive Ingredients

Citric Acid, Grape Flavor, Propylene Glycol, Purified Water, Saccharine Sodium, Sodium Benzoate, Sorbitol, Sucralose.

Other Information

Store at 20°-25°C (68°-77°F)

Tamper evident by seal under cap. Do not use if the seal is broken or missing.

PRINCIPAL DISPLAY PANEL - 473 mL Bottle Label

NDC-43913-407-16

G-Xpect PSE

Cough Suppressant, Expectorant & Nasal Decongestant

Sugar Free • Dye Free • Alcohol Free • Phenylalanine Free

Grape Flavor

16 FL OZ (473 mL)

Multiple Dose Unit Package
For Dispensing Under Pharmaceutical Supervision Only

McLaren Medical